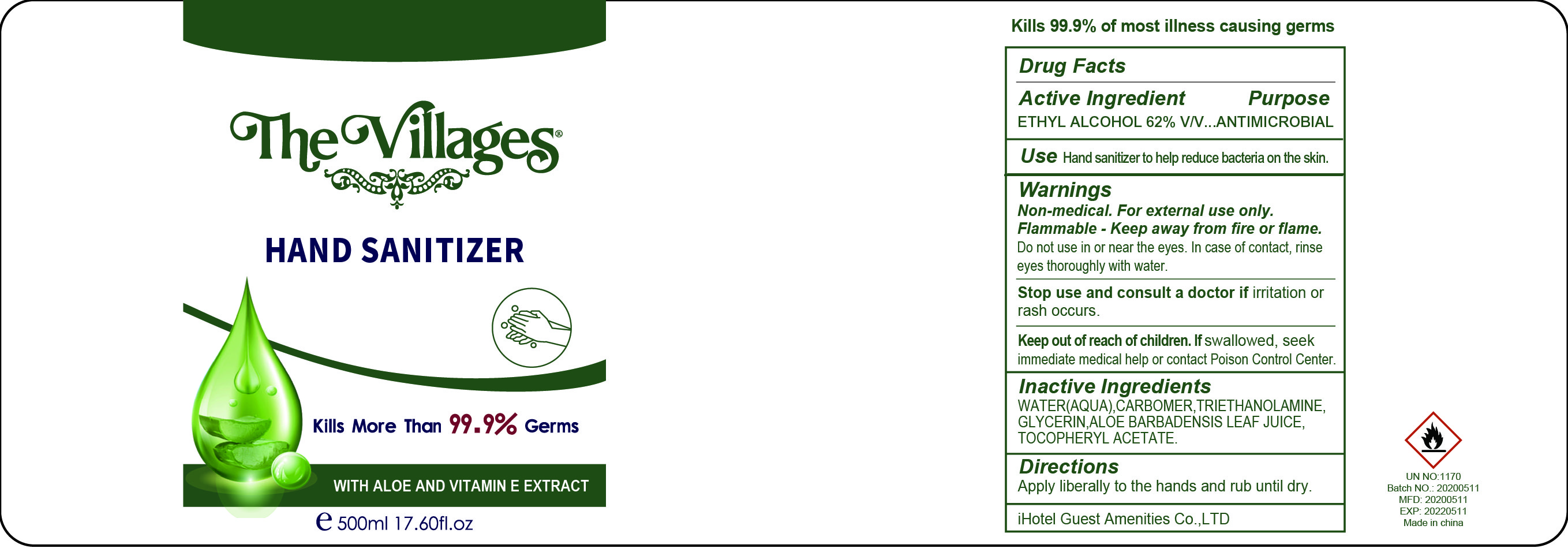 DRUG LABEL: The Villages Hand Sanitizer With Aloe and Vitamin E Extract
NDC: 71004-103 | Form: SOLUTION
Manufacturer: iHotel Guest Amenities Co.,Ltd
Category: otc | Type: HUMAN OTC DRUG LABEL
Date: 20200623

ACTIVE INGREDIENTS: ALCOHOL 62 mL/100 mL
INACTIVE INGREDIENTS: CARBOMER 934; TROLAMINE; GLYCERIN; .ALPHA.-TOCOPHEROL ACETATE; ALOE VERA LEAF

The villiages Hand Sanitizer

ACTIVE INGREDIENT

Ethyl Alcohol 62%

Purpose

Antimicrobial

Use

Hand sanitizer to help reduce bacteria on the skin

Warnings

For external use only.

Non Medical. Flammable. Keep away from fire or flame

Do not use in or near eyes, In case of contact, rinse thoroughly with water

Stop use and consult a doctor if irritation or rash occurs

Keep out of reach of children. If swallowed, seek immediate medical help or contact a poison control center

Directions

- Apply literally to the hands and rub until dry

Inactive ingredients

Water, Carbomer, Triethanolamine, Glycerin, Alor Barbardensis Leaf Juice, Tocopheryl Acetate